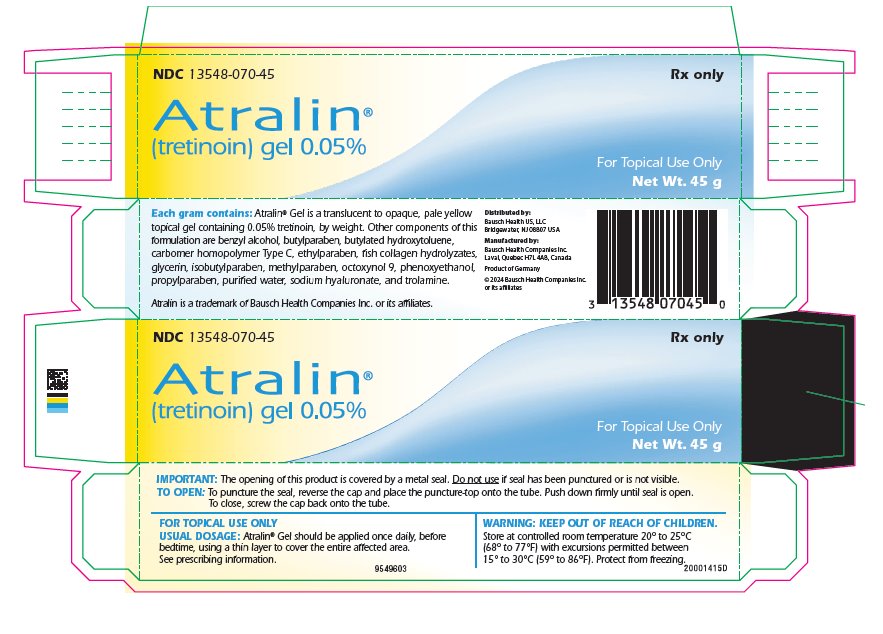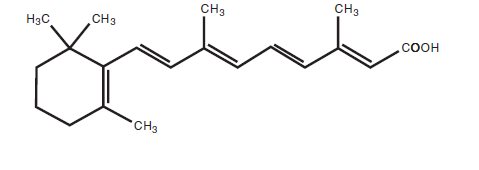 DRUG LABEL: Atralin
NDC: 13548-070 | Form: GEL
Manufacturer: Bausch Health US, LLC
Category: prescription | Type: HUMAN PRESCRIPTION DRUG LABEL
Date: 20240201

ACTIVE INGREDIENTS: Tretinoin 0.05 g/100 g
INACTIVE INGREDIENTS: benzyl alcohol; butylparaben; butylated hydroxytoluene; CARBOMER HOMOPOLYMER TYPE C (ALLYL PENTAERYTHRITOL CROSSLINKED); ethylparaben; MARINE COLLAGEN, SOLUBLE; glycerin; isobutylparaben; methylparaben; octoxynol-9; phenoxyethanol; propylparaben; water; hyaluronate sodium; trolamine

HIGHLIGHTS OF PRESCRIBING INFORMATION

These highlights do not include all the information needed to use ATRALIN Gel safely and effectively. See full prescribing information for ATRALIN Gel.
ATRALIN® (tretinoin) Gel, 0.05%, for topical use
Initial U.S. Approval: 1973

1 INDICATIONS AND USAGE

Atralin Gel is a retinoid indicated for topical treatment of acne vulgaris. (1)

2 DOSAGE AND ADMINISTRATION

- Apply a thin layer of Atralin Gel once daily, before bedtime, to skin where lesions occur. Keep away from eyes, mouth, nasal creases, and mucous membranes. (2)
- Atralin Gel is not for oral, ophthalmic, or intravaginal use. (2)

3 DOSAGE FORMS AND STRENGTHS

Gel, 0.05% (3)

4 CONTRAINDICATIONS

None (4)

5 WARNINGS AND PRECAUTIONS

- Atralin Gel should not be used on eczematous or sunburned skin due to potential for severe irritation. (5.1)
- Topical over-the-counter acne preparations, concomitant topical medications, medicated cleansers, topical products with alcohol or astringents: Use with caution, irritation may occur. (5.1)
- Avoid unprotected exposure to sunlight including sunlamps (UV light) when using Atralin Gel due to potential for increased photosensitization. Use sunscreen of at least SPF 15 and protective clothing during exposure. (5.2)
- Avoid use of Atralin Gel with weather extremes, such as wind or cold due to potential for increased irritation. (5.2)
- Use Atralin Gel with caution if allergic to fish due to potential for allergenicity to fish protein. Patients who develop pruritus or urticaria should contact their healthcare provider. (5.3)

6 ADVERSE REACTIONS

The most common adverse reactions (incidence ≥5%) with Atralin Gel are dry skin, peeling/scaling/flaking skin, skin burning sensation, and erythema. (6.1)

To report SUSPECTED ADVERSE REACTIONS, contact Bausch Health US, LLC at 1-800-321-4576 or FDA at 1-800-FDA-1088 or www.fda.gov/medwatch.

FULL PRESCRIBING INFORMATION

1 INDICATIONS AND USAGE

Atralin Gel is indicated for topical treatment of acne vulgaris.

2 DOSAGE AND ADMINISTRATION

For topical use only. Not for oral, ophthalmic, or intravaginal use.

Atralin Gel should be applied once daily, before bedtime, to the skin where acne lesions appear, using a thin layer to cover the entire affected area. Atralin Gel should be kept away from the eyes, the mouth, paranasal creases, and mucous membranes. Application of excessive amounts of gel will not provide incremental efficacy.

Patients treated with Atralin Gel may use cosmetics, but the areas to be treated should be cleansed thoroughly before the medication is applied.

When treating with Atralin Gel, caution should be exercised with the use of concomitant topical over-the-counter preparations, topical medications, medicated or abrasive soaps and cleansers, products that have strong drying effect, and products with high concentrations of alcohol, astringents, spices, or lime. Particular caution should be exercised with acne preparations containing benzoyl peroxide, sulfur, resorcinol, or salicylic acid. Allow the effects of such preparations to subside before use of Atralin Gel has begun.

3 DOSAGE FORMS AND STRENGTHS

Gel, 0.05%

Each gram of Atralin Gel contains 0.5 mg (0.05%) tretinoin in a translucent to opaque, pale yellow topical gel.

4 CONTRAINDICATIONS

None.

5 WARNINGS AND PRECAUTIONS

5.1 Skin Irritation

The skin of certain individuals may become dry, red, or exfoliated while using Atralin Gel. If the degree of irritation warrants, patients should be directed to temporarily reduce the amount or frequency of application of the medication, discontinue use temporarily, or discontinue use all together. Efficacy at reduced frequencies of application has not been established. If a reaction suggesting sensitivity occurs, use of the medication should be discontinued. Mild to moderate skin dryness may also be experienced; if so, use of an appropriate moisturizer during the day may be helpful.

Tretinoin has been reported to cause severe irritation on eczematous or sunburned skin and should be used with caution in patients with these conditions.

To help limit skin irritation, patients must:

- wash the treated skin gently, using a mild, non-medicated soap, and pat it dry,
- avoid washing the treated skin too often and scrubbing the affected skin area, and
- avoid contact with the peels of limes.

5.2 Ultraviolet Light and Environmental Exposure

Unprotected exposure to sunlight, including sunlamps, should be minimized during the use of Atralin Gel. Patients who normally experience high levels of sun exposure, and those with inherent sensitivity to sun, should be warned to exercise caution. Use of sunscreen products of at least SPF 15 and protective clothing over treated areas is recommended when exposure cannot be avoided.

Weather extremes, such as wind or cold, also may be irritating to tretinoin-treated skin.

5.3 Fish Allergies

Atralin Gel contains soluble fish proteins and should be used with caution in patients with known sensitivity or allergy to fish. Patients who develop pruritus or urticaria should contact their healthcare provider.

6 ADVERSE REACTIONS

6.1 Clinical Trials Experience

Because clinical trials are conducted under prescribing conditions, adverse reaction rates observed in the clinical trials of a drug cannot be directly compared to rates in the clinical trials of another drug and may not reflect the rates observed in practice.

In two randomized, controlled trials, 674 subjects received treatment for up to 12 weeks with Atralin Gel [see Clinical Studies (14)]. In these studies, 50% of the subjects who were treated with Atralin Gel reported one or more adverse reactions; 30% of the subjects reported treatment-related adverse reactions. In the vehicle group, 29% of the 487 randomized subjects reported at least one adverse reaction; 5% of the subjects reported events that were treatment-related. There were no serious, treatment-related adverse reactions reported by subjects in any of the treatment groups.

Selected adverse reactions that occurred in at least 1% of subjects in the two trials combined are shown in Table 1 (below). Most skin-related adverse reactions first appear during the first two weeks of treatment with Atralin Gel, and the incidence rate for skin-related reactions peaks around the second and third week of treatment. In some subjects, the skin-related adverse reactions persist throughout the treatment period.

Table 1: Number of Subjects with Selected Adverse Reactions (Occurring in at Least 1% of Subjects)
Event | Atralin Gel (N = 674) | Vehicle (N = 487)
Dry Skin | 109 (16%) | 8 (2%)
Peeling/Scaling/Flaking Skin | 78 (12%) | 7 (1%)
Skin Burning Sensation | 53 (8%) | 8 (2%)
Erythema | 47 (7%) | 1 (<1%)
Pruritus | 11 (2%) | 3 (1%)
Pain of Skin | 7 (1%) | 0 (0%)
Sunburn | 7 (1%) | 3 (1%)

6.2 Postmarketing Experience

The following adverse reactions have been identified during post-approval use of Atralin Gel. Because these reactions are reported voluntarily from a population of uncertain size, it is not always possible to reliably estimate their frequency or establish a causal relationship to drug exposure.

Temporary hyper- or hypopigmentation has been reported with repeated application of tretinoin.

8 USE IN SPECIFIC POPULATIONS

8.1 Pregnancy

TERATOGENIC EFFECTS

There are no well-controlled trials in pregnant women treated with Atralin Gel. Atralin Gel should be used during pregnancy only if the potential benefit justifies the potential risk to the fetus.

Atralin Gel at doses of 0.1, 0.3 and 1 g/kg/day was tested for maternal and developmental toxicity in pregnant Sprague-Dawley rats by dermal application. The dose of 1 g/kg/day was approximately four times the clinical dose assuming 100% absorption and based on body surface area comparison. Possible tretinoin-associated teratogenic effects (craniofacial abnormalities [hydrocephaly], asymmetrical thyroids, variations in ossification, and increased supernumerary ribs) were noted in the fetuses of Atralin Gel-treated animals. These findings were not observed in control animals. Other maternal and reproductive parameters in the Atralin Gel-treated animals were not different from control. For purposes of comparison of the animal exposure to human exposure, the clinical dose is defined as 2 g of Atralin Gel applied daily to a 50 kg person.

Oral tretinoin has been shown to be teratogenic in rats, mice, rabbits, hamsters and nonhuman primates. Tretinoin was teratogenic in Wistar rats when given orally in doses greater than 1 mg/kg/day (approximately eight times the clinical dose based on body surface area comparison). In the cynomolgus monkey, fetal malformations were reported for doses of 10 mg/kg/day, but none were observed at 5 mg/kg/day (approximately 80 times the clinical dose based on body surface area comparison), although increased skeletal variations were observed at all doses. Dose-related increases in embryolethality and abortion also were reported. Similar results have also been reported in pigtail macaques.

Topical tretinoin in a different formulation has generated equivocal results in animal teratogenicity tests. There is evidence for teratogenicity (shortened or kinked tail) of topical tretinoin in Wistar rats at doses greater than 1 mg/kg/day (approximately eight times the clinical dose assuming 100% absorption and based on body surface area comparison). Anomalies (humerus: short 13%, bent 6%, os parietal incompletely ossified 14%) have also been reported when 10 mg/kg/day (approximately 160 times the clinical dose assuming 100% absorption and based on body surface area comparison) was topically applied. Supernumerary ribs have been a consistent finding in rats when dams were treated topically or orally with retinoids.

With widespread use of any drug, a small number of birth defect reports associated temporally with the administration of the drug would be expected by chance alone. Cases of temporally associated congenital malformations have been reported with use of other topical tretinoin products. The significance of these spontaneous reports in terms of risk to the fetus is not known.

Nonteratogenic Effects on Fetuses: Oral tretinoin has been shown to be fetotoxic in rats when administered in doses 20 times the clinical dose based on body surface area comparison. Topical tretinoin has been shown to be fetotoxic in rabbits when administered in doses eight times the clinical dose based on body surface area comparison.

8.3 Nursing Mothers

It is not known whether this drug is excreted in human milk. Because many drugs are excreted in human milk, caution should be exercised when Atralin Gel is administered to a nursing woman.

8.4 Pediatric Use

Safety and effectiveness in children below the age of 10 have not been established.

A total of 381 pediatric subjects (aged 10 to 16 years) treated with Atralin Gel were enrolled into the two clinical studies. Across these two studies, comparable safety and efficacy were observed between pediatric and adult subjects.

8.5 Geriatric Use

Safety and effectiveness in a geriatric population have not been established. Clinical studies of Atralin Gel did not include any subjects over age 65 to determine whether they respond differently from younger subjects.

11 DESCRIPTION

Atralin (tretinoin) Gel, 0.05% is a translucent to opaque, pale yellow gel containing 0.05% tretinoin, by weight for topical administration.

Chemically, tretinoin is all-trans-retinoic acid, also known as (all-E)-3,7-dimethyl-9-(2,6,6-trimethyl-1-cyclohexen-1-yl)-2,4,6,8-nonatetraenoic acid. It is a member of the retinoid class of compounds, and a metabolite of Vitamin A. Tretinoin has a molecular weight of 300.44, a molecular formula of C20H28O2 and the following structure:

Each gram of Atralin Gel, 0.05% contains 0.5 mg of tretinoin.

Other components of this formulation are benzyl alcohol, butylparaben, butylated hydroxytoluene, carbomer homopolymer Type C, ethylparaben, fish collagen hydrolyzates, glycerin, isobutylparaben, methylparaben, octoxynol 9, phenoxyethanol, propylparaben, purified water, sodium hyaluronate, and trolamine. The contribution to efficacy of individual components of the vehicle has not been evaluated.

12 CLINICAL PHARMACOLOGY

12.1 Mechanism of Action

Tretinoin is a metabolite of Vitamin A that binds with high affinity to specific retinoic acid receptors located in both the cytosol and nucleus, but cutaneous levels of tretinoin in excess of physiologic concentrations occur following application of a tretinoin-containing topical drug product.

Although tretinoin activates three members of the retinoid acid (RAR) nuclear receptors (RARα, RARβ, and RARγ) which act to modify gene expression, subsequent protein synthesis, and epithelial cell growth and differentiation, it has not been established whether the clinical effects of tretinoin are mediated through activation of retinoic acid receptors, other mechanisms, or both.

Although the exact mode of action of tretinoin is unknown, current evidence suggests that topical tretinoin decreases cohesiveness of follicular epithelial cells with decreased microcomedo formation. Additionally, tretinoin stimulates mitotic activity and increased turnover of follicular epithelial cells causing extrusion of the comedones.

12.3 Pharmacokinetics

In two studies, the plasma levels of tretinoin and its major metabolites (13-cis-retinoic acid and 4-oxo-13-cis-retinoic acid) were investigated in a total of 14 patients (age: 13 – 25 years) with severe acne, who applied 4 g ± 0.5 g (range 3.5 g – 4.5 g) of Atralin Gel once daily to face, back and chest, as compared to a mean of 0.71 g (range of 0.07 – 3.71 g) applied in the controlled clinical trials. Blood samples were taken at baseline and immediately prior to treatment on Days 1, 5, 10 and 14. On Day 14, the final study day, samples also were taken 1, 2, 4, 6, 8, 10, 12, 16, and 24 hours post-treatment.

The plasma concentrations of tretinoin and its metabolites could be measured (LOQ = 0.5 ng/mL for all three analytes) in all patients at all time points. The range of plasma concentrations of tretinoin and its metabolites, 13-cis-retinoic acid and all-trans-4-oxo-retinoic acid at baseline and after multiple once-daily applications of Atralin Gel, 0.05% for 14 days are given in Table 2 (below). Although some patients had increased concentrations of tretinoin or its metabolites over baseline values, no consistent increase in these concentrations were observed across patients.

Table 2: Concentrations of Active and Metabolites at Baseline and at Day 14 After Exposure to Atralin Gel, 0.05%
Compound | Baseline Concentration Range (ng/mL) | Day 14 Concentration Range (ng/mL)
Tretinoin | 0.68-1.62 | 0.69-2.88
13-cis-retinoic acid | 0.67-1.79 | 0.51-2.26
4-oxo-13-cis-retinoic acid | 0.82-5.92 | 0.59-6.96

13 NONCLINICAL TOXICOLOGY

13.1 Carcinogenesis, Mutagenesis, Impairment of Fertility

A 2-year dermal mouse carcinogenicity study was initiated with topical administration of 0.005%, 0.025% and 0.05% Atralin Gel. Although no drug-related tumors were observed in surviving animals, the irritating nature of the drug product precluded daily dosing, confounding data interpretation and reducing the biological significance of these results.

Studies in hairless albino mice with a different formulation suggest that concurrent exposure to tretinoin may enhance the tumorigenic potential of carcinogenic doses of UVB and UVA light from a solar simulator. This effect was confirmed in a later study in pigmented mice, and dark pigmentation did not overcome the enhancement of photocarcinogenesis by 0.05% tretinoin. Although the significance of these studies to humans is not clear, patients should minimize exposure to sunlight or artificial ultraviolet irradiation sources.

The genotoxic potential of tretinoin was evaluated in an in vitro bacterial reversion test, an in vitro chromosomal aberration assay in human lymphocytes and an in vivo rat micronucleus assay. All tests were negative.

In dermal fertility studies of another tretinoin formulation in rats, slight (not statistically significant) decreases in sperm count and motility were seen at 0.5 mg/kg/day (3 mg/m^2, approximately four times the clinical dose based on body surface area comparison), and slight (not statistically significant) increases in the number and percent of nonviable embryos in females treated with 0.25 mg/kg/day and above (1.5 mg/m^2, approximately two times the clinical dose based on body surface area comparison) were observed.

14 CLINICAL STUDIES

The safety and efficacy of Atralin Gel used once daily before bedtime for the treatment of mild to moderate acne vulgaris were assessed in two 12-week prospective, multicenter, randomized, controlled trials. Subjects in these two trials ranged from 10 to 65 years of age, were approximately 52% female, 48% male, and were 74% Caucasian, 15% Black or African American, 3% Asian, and 8% Other.

Efficacy results at Week 12 are presented in Table 3. Success on the 6-point Global Severity Score is defined as a score of 0 (clear) or 1 (very mild). In Trial 2, subjects were also required to have at least two grades reduction from baseline for success. ‘Very mild’ acne is defined as: skin almost clear; rare non-inflammatory lesions present, with rare non-inflamed papules (papules may be hyperpigmented, though not pink-red, less than 4 lesions). The database was not large enough to assess whether there were differences in effects in age, gender, or race subgroups.

Table 3: Efficacy Results at Week 12 in Trials 1 and 2
Trial 1 | Atralin Gel (N=375) | Vehicle (N=185)
Global Severity Score Success [Success was defined as 0 (clear) or 1 (very mild)] | 78 (21%) | 23 (12%)
Non-Inflammatory Facial Lesions
Mean Baseline Count | 50.7 | 52.4
Mean Absolute Reduction | 21.8 | 10.3
Mean Percent Reduction | 43% | 21%
Inflammatory Facial Lesions
Mean Baseline Count | 23.4 | 23.9
Mean Absolute Reduction | 9.7 | 5.8
Mean Percent Reduction | 41% | 26%
Total Facial Lesions
Mean Baseline Count | 74.1 | 76.3
Mean Absolute Reduction | 31.4 | 16.1
Mean Percent Reduction | 43% | 22%
Trial 2 | Atralin Gel (N=299) | Vehicle (N=302)
Global Severity Score Success [Success was defined as 0 (clear) or 1 (very mild) with at least two grades reduction from baseline] | 69 (23%) | 42 (14%)
Non-Inflammatory Facial Lesions
Mean Baseline Count | 51.9 | 52.7
Mean Absolute Reduction | 18.7 | 10.8
Mean Percent Reduction | 37% | 20%
Inflammatory Facial Lesions
Mean Baseline Count | 22.9 | 23.4
Mean Absolute Reduction | 7.0 | 4.0
Mean Percent Reduction | 30% | 17%
Total Facial Lesions
Mean Baseline Count | 74.8 | 76.1
Mean Absolute Reduction | 25.7 | 14.7
Mean Percent Reduction | 35% | 19%

16 HOW SUPPLIED/STORAGE AND HANDLING

Atralin (tretinoin) Gel, 0.05% is a translucent to opaque, pale yellow topical gel and available as:

- 45 g tube NDC 13548-070-45

Storage and Handling: Store at controlled room temperature 20° to 25°C (68° to 77°F) with excursions permitted between 15° to 30°C (59° to 86°F). Protect from freezing. Keep out of reach of children.

17 PATIENT COUNSELING INFORMATION

Advise the patient to read the FDA-approved patient labeling (Patient Information).

Instruct patients to clean the affected areas with an appropriate cleanser before applying Atralin Gel.

Patients may use moisturizers that are noncomedogenic and should avoid products that could be drying or irritating.

Patients may also wear cosmetics while being treated with Atralin Gel; however, they should be instructed to remove the cosmetics and clean the area thoroughly before applying Atralin Gel.

Warn patients of the drying and irritation effects often seen during treatment. Continue use of the medication if these effects are tolerable.

Caution patients against application of Atralin Gel around the eyes, mouth, paranasal creases, and mucous membranes as the skin is especially prone to irritation.

Minimize exposure to sunlight, including sunlamps. Recommend the use of sunscreen products and protective apparel (e.g., hat) when exposure cannot be avoided.

Distributed by:

Bausch Health US, LLC

Bridgewater, NJ 08807 USA

Manufactured by:

Bausch Health Companies Inc.

Laval, Quebec H7L 4A8, Canada

Atralin is a trademark of Bausch Health Companies Inc. or its affiliates.

All other product/brand names and/or logos are trademarks of the respective owners.

© 2024 Bausch Health Companies Inc. or its affiliates

9549701

Patient Information
Atralin® (A-truh-lin)
(tretinoin) Gel, 0.05%
for topical use

Important information: Atralin is for use on skin only. Do not get Atralin in your mouth, eyes, vagina, or the corners of your nose.

What is Atralin?

Atralin is a prescription medicine used on the skin (topical) to treat acne. Acne is a condition in which the skin has blackheads, whiteheads, and other pimples.

It is not known if Atralin is safe and effective in children under 10 years of age.

What should I tell my healthcare provider before using Atralin?

Before using Atralin, tell your healthcare provider about all of your medical conditions, including if you:

- are allergic to fish. Atralin contains fish proteins. Tell your healthcare provider if you get hives or itching during treatment with Atralin.
- have a skin condition called eczema.
- have a sunburn.
- are pregnant or plan to become pregnant. It is not known if Atralin will harm your unborn baby.
- are breastfeeding or plan to breastfeed. It is not known if Atralin passes into your breast milk.

Tell your healthcare provider about all the medicines you take, including prescription and over-the-counter medicines, vitamins, herbal supplements, and any skin products that you use.

Especially tell your healthcare provider if you use any other medicines to treat your acne, including medicated cleansers or soaps. Using other topical acne products may increase the irritation of your skin when used with Atralin.

How should I use Atralin?

- Use Atralin exactly as your healthcare provider tells you to use it.
- Before you apply Atralin, gently wash the affected skin area with a mild, non-medicated soap. Rinse and pat your skin dry.
- Apply Atralin 1 time a day before bedtime.
- Apply a thin layer of Atralin to cover the affected skin areas. Gently rub Atralin into your skin.
- Do not use more Atralin than you need to cover the affected area and do not apply Atralin more than 1 time a day. Using too much Atralin may irritate or increase the irritation of your skin, and will not give faster or better results.
- You may use moisturizers and cosmetics.

What should I avoid while using Atralin?

- Avoid washing your skin too often and scrubbing the affected skin area.
- You should avoid sunlamps, tanning beds, and ultraviolet light during treatment with Atralin.
- Minimize exposure to sunlight.
- If you have to be in the sunlight or are sensitive to sunlight, use a sunscreen with a (SPF) sun protection factor of 15 or more and wear protective clothing, and a wide brimmed hat to cover the treated areas.
- If you do get sunburned, stop using Atralin until your skin has healed and is back to normal.
- Cold weather and wind may irritate skin treated with Atralin. Skin treated with Atralin may dry out or get wind burned more easily. Talk to your healthcare provider about ways to manage skin irritation.
- Avoid contact with the peels of limes.

What are the possible side effects of Atralin?

Atralin may cause skin irritation, including: skin dryness, burning, redness, excessive flaking or peeling. If you develop these symptoms, your healthcare provider may tell you to stop using Atralin for a while, decrease the number of times you apply Atralin, or completely stop treatment with Atralin. It is not known if Atralin is effective when used less than 1 time a day.

Tell your healthcare provider if you have any side effect that bothers you or that does not go away. These are not all of the side effects possible with Atralin.

Call your doctor for medical advice about side effects. You may report side effects to FDA at 1-800-FDA-1088.

How should I store Atralin?

- Store Atralin at room temperature, 68°F to 77°F (20°C to 25°C).
- Protect from freezing.

Keep Atralin and all medicines out of the reach of children.

General information about the safe and effective use of Atralin

Medicines are sometimes prescribed for purposes other than those listed in a Patient Information leaflet. Do not use Atralin for a condition for which it was not prescribed. Do not give Atralin to other people, even if they have the same symptoms you have. It may harm them.

You can ask your pharmacist or healthcare provider for information about Atralin that is written for health professionals.

What are the ingredients of Atralin?

Active ingredient: tretinoin
Inactive ingredients: benzyl alcohol, butylparaben, butylated hydroxytoluene, carbomer homopolymer Type C, ethylparaben, fish collagen hydrolyzates, glycerin, isobutylparaben, methylparaben, octoxynol 9, phenoxyethanol, propylparaben, purified water, sodium hyaluronate, and trolamine.

Distributed by:

Bausch Health US, LLC

Bridgewater, NJ 08807 USA

Manufactured by:

Bausch Health Companies Inc.

Laval, Quebec H7L 4A8, Canada

For more information, call 1-800-321-4576.

Atralin is a trademark of Bausch Health Companies Inc. or its affiliates.

All other product/brand names and/or logos are trademarks of the respective owners.

© 2024 Bausch Health Companies Inc. or its affiliates

This Patient Information has been approved by the U.S. Food and Drug Administration.

Rev. 02/2024 9549701

PACKAGE LABEL

PRINCIPAL DISPLAY PANEL - 45 g Tube Carton

NDC 13548-070-45

Atralin®
(tretinoin) gel 0.05%

Rx only

Net Wt. 45 g